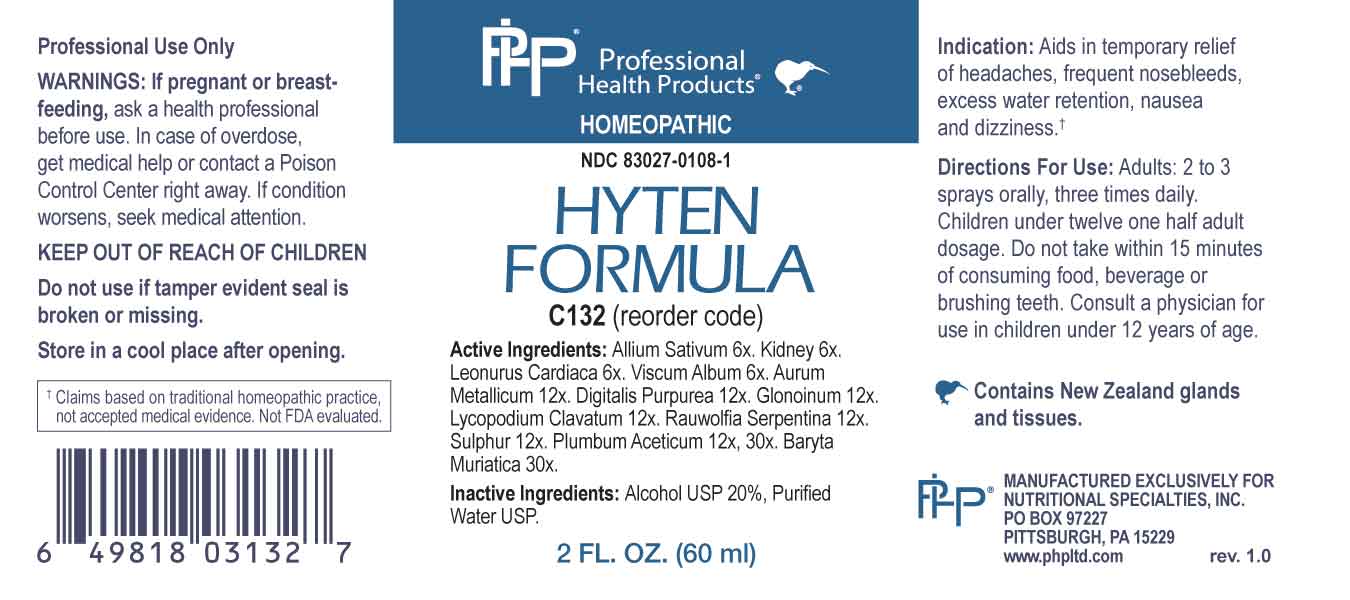 DRUG LABEL: Hyten Formula
NDC: 83027-0108 | Form: SPRAY
Manufacturer: Nutritional Specialties, Inc.
Category: homeopathic | Type: HUMAN OTC DRUG LABEL
Date: 20230928

ACTIVE INGREDIENTS: GARLIC 6 [hp_X]/1 mL; BEEF KIDNEY 6 [hp_X]/1 mL; LEONURUS CARDIACA WHOLE 6 [hp_X]/1 mL; VISCUM ALBUM FRUITING TOP 6 [hp_X]/1 mL; GOLD 12 [hp_X]/1 mL; DIGITALIS 12 [hp_X]/1 mL; NITROGLYCERIN 12 [hp_X]/1 mL; LYCOPODIUM CLAVATUM SPORE 12 [hp_X]/1 mL; RAUWOLFIA SERPENTINA 12 [hp_X]/1 mL; SULFUR 12 [hp_X]/1 mL; LEAD ACETATE ANHYDROUS 12 [hp_X]/1 mL; BARIUM CHLORIDE DIHYDRATE 30 [hp_X]/1 mL
INACTIVE INGREDIENTS: WATER; ALCOHOL

DRUG FACTS:

ACTIVE INGREDIENTS:

Allium Sativum 6X, Kidney 6X, Leonurus Cardiaca 6X, Viscum Album 6X, Aurum Metallicum 12X, Digitalis Purpurea 12X, Glonoinum 12X, Lycopodium Clavatum 12X, Rauwolfia Serpentina 12X, Sulphur 12X, Plumbum Aceticum 12X, 30X, Baryta Muriatica 30X.

PURPOSE:

Aids in temporary relief of headaches, frequent nosebleeds, excess water retention, nausea and dizziness.†

†Claims based on traditional homeopathic practice, not accepted medical evidence. Not FDA evaluated.

WARNINGS:

Professional Use Only

If pregnant or breast-feeding, ask a health professional before use.

In case of overdose, get medical help or contact a Poison Control Center right away.

If condition worsens, seek medical attention.

KEEP OUT OF REACH OF CHILDREN

Do not use if tamper evident seal is broken or missing.

Store in a cool place after opening

KEEP OUT OF REACH OF CHILDREN:

In case of overdose, get medical help or contact a Poison Control Center right away.

DIRECTIONS:

Adults: 2 to 3 sprays orally, three times daily. Children under twelve one half adult dosage. Do not take within 15 minutes of consuming food, beverage or brushing teeth. Consult a physician for use in children under 12 years of age.

INDICATIONS

Aids in temporary relief of headaches, frequent nosebleeds, excess water retention, nausea and dizziness.†

†Claims based on traditional homeopathic practice, not accepted medical evidence. Not FDA evaluated.

INACTIVE INGREDIENTS:

Alcohol USP 20%, Purified Water USP.

QUESTIONS:

MANUFACTURED EXCLUSIVELY FOR

NUTRITIONAL SPECIALTIES, INC.

PO BOX 97227

PITTSBURG, PA 15229

www.phpltd.com

PACKAGE LABEL DISPLAY:

Professional

Health Products

HOMEOPATHIC

NDC 83027-0108-1

HYTEN

FORMULA

2 FL. OZ (60 ml)